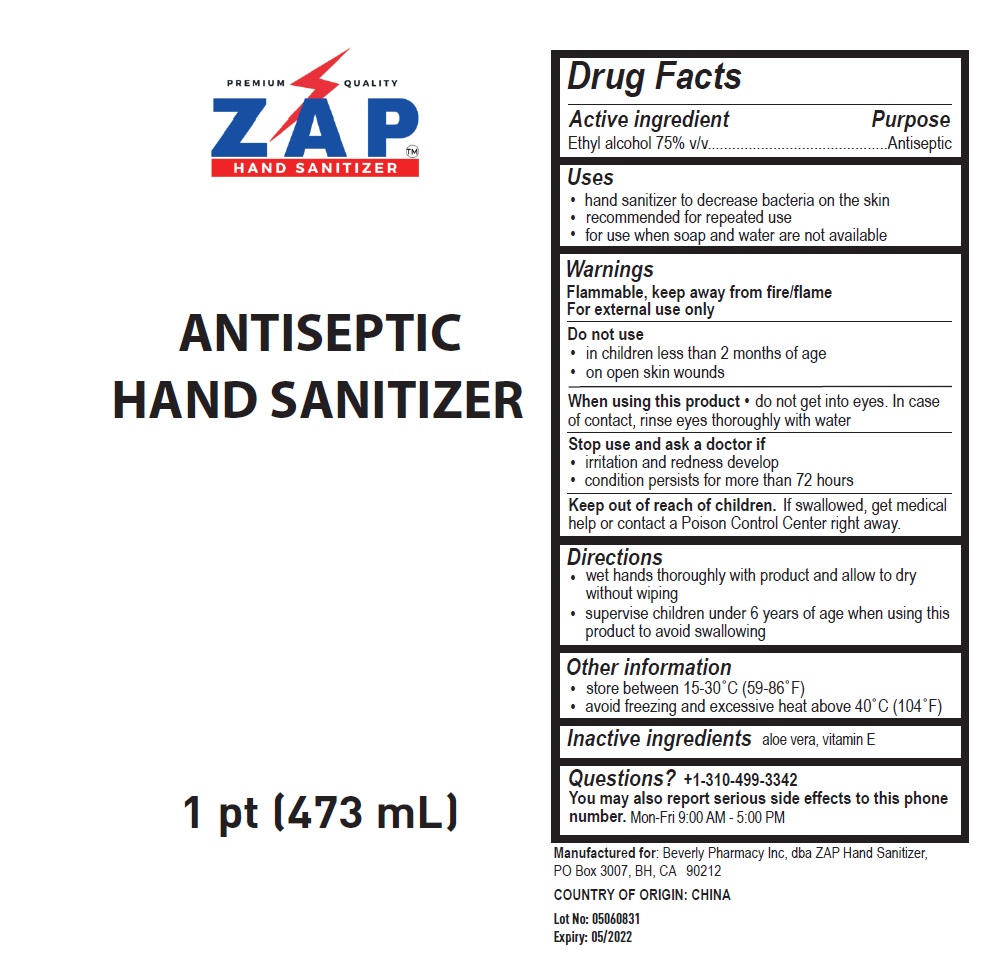 DRUG LABEL: ZAP Hand Sanitizer
NDC: 90041-800 | Form: LIQUID
Manufacturer: Beverly Pharmacy, Inc. Dba Zap Hand Sanitizer
Category: otc | Type: HUMAN OTC DRUG LABEL
Date: 20200819

ACTIVE INGREDIENTS: ALCOHOL 75 mL/100 mL
INACTIVE INGREDIENTS: ALOE VERA LEAF; .ALPHA.-TOCOPHEROL

PREMIUM QUALITY ZAP™ HAND SANITIZER

Active ingredient

Ethyl alcohol 75% v/v

Purpose

Antiseptic

Uses

- hand sanitizer to decrease bacteria on the skin
- recommended for repeated use
- for use when soap and water are not available

Warnings

Flammable, keep away from fire/flame

For external use only

Do not use

• in children less than 2 months of age

• on open skin wounds

When using this product • do not get into eyes. In case of contact, rinse eyes thoroughly with water

Stop use and ask a doctor if

• irritation and redness develop

• condition persists for more than 72 hours

Keep out of reach of children. If swallowed, get medical help or contact a Poison Control Center right away.

Directions

- wet hands thoroughly with product and allow to dry without wiping
- supervise children under 6 years of age when using this product to avoid swallowing

Other information

- store between 15-30°C (59-86°F)
- avoid freezing and excessive heat above 40°C (104°F)

Inactive ingredients aloe vera, vitamin E

Questions? +1-310-499-3342

You may also report serious side effects to this phone number. Mon-Fri 9:00 AM - 5:00 PM

ANTISEPTIC HAND SANITIZER

Manufactured for: Beverly Pharmacy Inc, dba ZAP Hand Sanitizer, PO Box 3007, BH, CA 90212

COUNTRY OF ORIGIN: CHINA